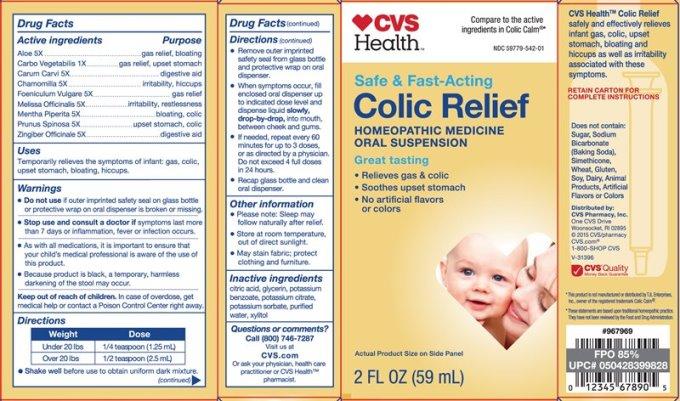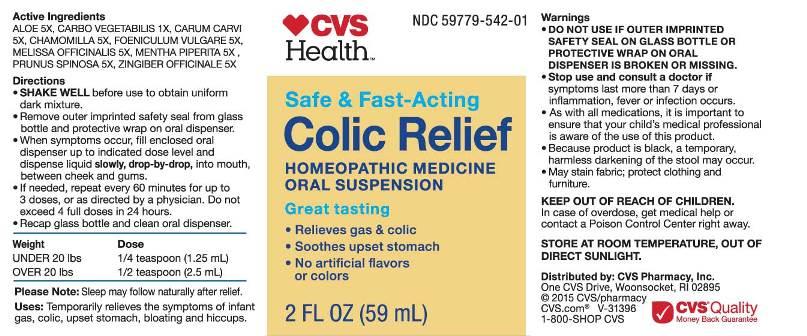 DRUG LABEL: Colic Relief
NDC: 59779-542 | Form: LIQUID
Manufacturer: CVS Pharmacy
Category: homeopathic | Type: HUMAN OTC DRUG LABEL
Date: 20160211

ACTIVE INGREDIENTS: ALOE 5 [hp_X]/1 mL; ACTIVATED CHARCOAL 1 [hp_X]/1 mL; CARAWAY SEED 5 [hp_X]/1 mL; MATRICARIA RECUTITA 5 [hp_X]/1 mL; FENNEL SEED 5 [hp_X]/1 mL; MELISSA OFFICINALIS 5 [hp_X]/1 mL; MENTHA PIPERITA 5 [hp_X]/1 mL; PRUNUS SPINOSA FLOWER BUD 5 [hp_X]/1 mL; GINGER 5 [hp_X]/1 mL
INACTIVE INGREDIENTS: CITRIC ACID MONOHYDRATE; GLYCERIN; POTASSIUM BENZOATE; POTASSIUM CITRATE; POTASSIUM SORBATE; WATER; XYLITOL

Drug Facts:

ACTIVE INGREDIENTS:

Aloe 5X, Carbo Vegetabilis 1X, Carum Carvi 5X, Chamomilla 5X, Foeniculum Vulgare 5X, Melissa Officinale 5X, Mentha Piperita 5X, Prunus Spinosa 5X, Zingiber Officinale5X.

USES:

Temporarily relieves the symptoms of infant gas, colic, upset stomach, bloating, hiccups.

WARNINGS:

• DO NOT USE IF OUTER IMPRINTED SAFETY SEAL ON GLASS BOTTLE OR PROTECTIVE WRAP ON ORAL DISPENSER ARE BROKEN OR MISSING.

• Stop use and consult a doctor if symptoms last more than 7 days or inflammation, fever or infection occurs.

• As with all medications, it is important to ensure that your child's medical professional is aware of the use of this product.

• Because product is black, a temporarily, harmless, darkening of the stool may occur.

• May stain fabric; protect clothing and furniture.

KEEP OUT OF REACH OF CHILDREN:

In case of overdose, get medical help or contact a Poison Control Center right away.

DIRECTIONS:

• SHAKE WELL before use to obtain uniform dark mixture.
• Remove outer imprinted safety seal from glass bottle and protective wrap on oral dispenser.
• When symptoms occur, fill enclosed oral dispenser up to indicated dose level and dispense liquid slowly, drop-by-drop into mouth, between cheek and gums.
• If needed, repeat every 30 minutes for up to 3 doses, or as directed by a physician. Do not exceed 4 full doses in 24 hours.
• Recap glass bottle and clean oral dispenser.

Weight Dose
Under 20 lbs. 1/4 teaspoon (1.25 mL)
Over 20 lbs. 1/2 teaspoon (2.5 mL)

OTHER SAFETY INFORMATION:

Please note: Sleep may follow naturally after relief.

STORE AT ROOM TEMPERATURE, OUT OF DIRECT SUNLIGHT.

INDICATIONS:

Temporarily relieves the symptoms of infant gas, colic, upset stomach, bloating, hiccups.

INACTIVE INGREDIENTS:

Citric Acid, Glycerin, Potassium Benzoate, Potassium Citrate, Potassium Sorbate, Purified Water, Xylitol.

QUESTIONS:

Distributed by: CVS Pharmacy, Inc.

One CVS Drive, Woonsocket, RI 02895

©2015 CVS/Pharmacy

CVS.com

1-800-SHOP CVS

PACKAGE LABEL DISPLAY:

CVS NDC 59779-542-01
Health

Safe & Fast-Acting
Colic Relief
HOMEOPATHIC MEDICINE
ORAL SUSPENSION
Great Tasting
• Relieves gas & Colic
• Soothes upset stomach
• No artificial flavors
or colors

2 FL OZ (59 mL)